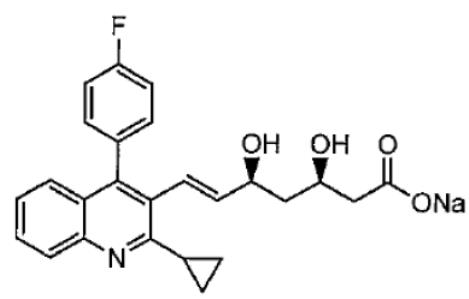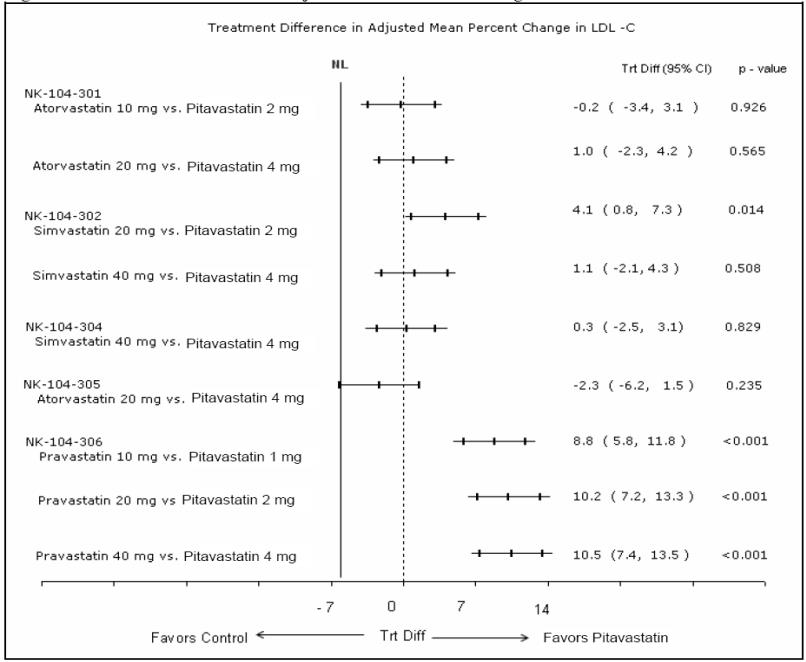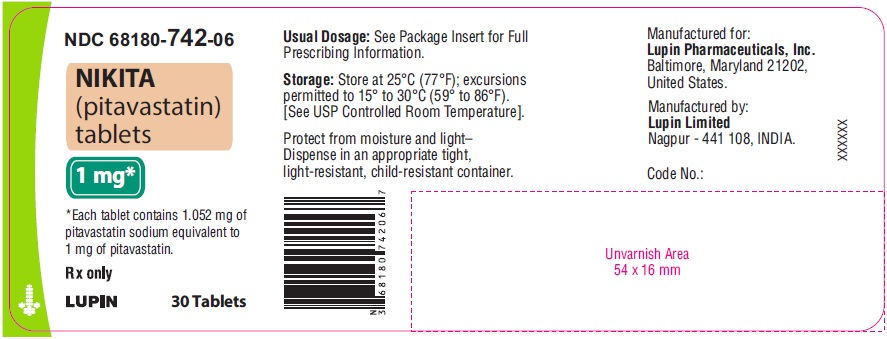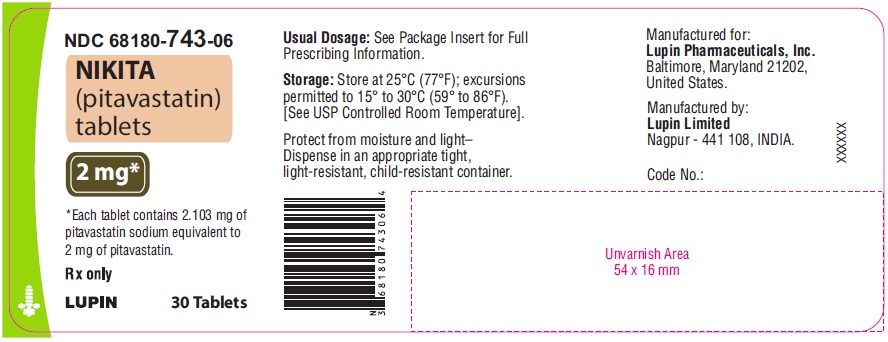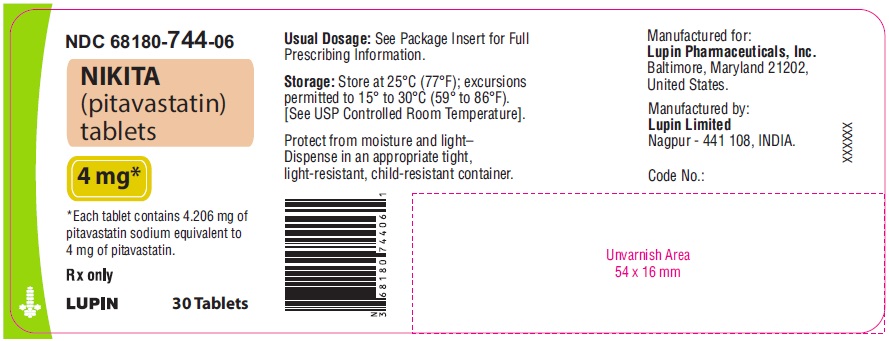 DRUG LABEL: NIKITA
NDC: 68180-742 | Form: TABLET
Manufacturer: Lupin Pharmaceuticals, Inc.
Category: prescription | Type: HUMAN PRESCRIPTION DRUG LABEL
Date: 20230630

ACTIVE INGREDIENTS: PITAVASTATIN 1 mg/1 1
INACTIVE INGREDIENTS: HYDROXYPROPYL CELLULOSE, LOW SUBSTITUTED; HYPROMELLOSE 2910 (5 MPA.S); HYPROMELLOSE 2910 (6 MPA.S); LACTOSE MONOHYDRATE; MAGNESIUM STEARATE; SILICON DIOXIDE; SODIUM BICARBONATE; TITANIUM DIOXIDE; TRIETHYL CITRATE

HIGHLIGHTS OF PRESCRIBING INFORMATION

These highlights do not include all the information needed to use NIKITA safely and effectively. See full prescribing information for NIKITA.
NIKITA (pitavastatin) tablet, for oral use
Initial U.S. Approval: 2009

RECENT MAJOR CHANGES

Contraindications, Pregnancy and Lactation (4) Removed11/2022

Warnings and Precautions, Immune-Mediated Necrotizing Myopathy (5.2) 11/2022

1 INDICATIONS AND USAGE

NIKITA is a HMG-CoA reductase inhibitor (statin) indicated as an adjunct to diet to reduce low-density lipoprotein cholesterol (LDL-C) in: (1)

- Adults with primary hyperlipidemia.

2 DOSAGE AND ADMINISTRATION

- Take orally once daily with or without food at the same time each day. (2.1)
- For patients requiring a high-intensity statin or are unable to achieve their LDL-C goal receiving NIKITA 4 mg daily, prescribe alternative LDL-C-lowering treatment. (2.1)
- Assess LDL-C when clinically appropriate, as early as 4 weeks after initiation of NIKITA, and adjust the dosage if necessary. (2.1)
- Recommended dosage is 2 mg to 4 mg once daily. Maximum recommended dosage is 4 mg once daily. (2.2)
- Recommended starting dosage for patients with moderate and severe renal impairment and end-stage renal disease on hemodialysis is 1 mg once daily. Maximum recommended dosage is 2 mg once daily. (2.3)
- See full prescribing information for NIKITA dosage modifications due to drug interactions. (2.4)

3 DOSAGE FORMS AND STRENGTHS

- Tablets: 1 mg, 2 mg, and 4 mg (3)

4 CONTRAINDICATIONS

- Cyclosporine (4, 7)
- Active liver failure or decompensated cirrhosis (4, 5.3)
- Hypersensitivity to pitavastatin or any excipients in NIKITA (4)

5 WARNINGS AND PRECAUTIONS

- Myopathy and Rhabdomyolysis:Risk factors include age 65 or greater, uncontrolled hypothyroidism, renal impairment, concomitant use with certain other drugs, and higher NIKITA dosage. Discontinue NIKITA if markedly elevated CK levels occur or myopathy is diagnosed or suspected. Temporarily discontinue NIKITA in patients experiencing an acute or serious condition at high risk of developing renal failure secondary to rhabdomyolysis. Inform patients of the risk of myopathy and rhabdomyolysis when starting or increasing the NIKITA dosage. Instruct patients to promptly report unexplained muscle pain, tenderness or weakness particularly if accompanied by malaise or fever. (5.1, 7, 8.5, 8.6)
- Immune-Mediated Necrotizing Myopathy (IMNM):Rare reports of IMNM, an autoimmune myopathy, have been reported. Discontinue NIKITA if IMNM is suspected. (5.2)
- Hepatic Dysfunction: Increases in serum transaminases have occurred, some persistent. Rare reports of fatal and non-fatal hepatic failure have occurred. Consider testing liver enzymes before initiating therapy and as clinically indicated thereafter. If serious hepatic injury with clinical symptoms and/or hyperbilirubinemia or jaundice occurs, promptly discontinue NIKITA. (5.3)

6 ADVERSE REACTIONS

The most frequent adverse reactions (rate ≥ 2%) were myalgia, constipation, diarrhea, back pain, and pain in extremity. (6)

To report SUSPECTED ADVERSE REACTIONS, contact Lupin Pharmaceuticals, Inc. at 1-800-399-2561 or FDA at 1-800-FDA-1088 or www.fda.gov/medwatch.

7 DRUG INTERACTIONS

- See full prescribing information for details regarding concomitant use of NIKITA with other drugs that increase the risk of myopathy and rhabdomyolysis. (2.4, 7)

8 USE IN SPECIFIC POPULATIONS

- Pregnancy:May cause fetal harm. (8.1)
- Lactation: Breastfeeding not recommended during treatment with NIKITA. (8.2)

Pediatric use information is approved for Kowa Co Ltd's LIVALO (pitavastatin) tablets. However, due to Kowa Co Ltd's marketing exclusivity rights, this drug product is not labeled with that information.

FULL PRESCRIBING INFORMATION

1 INDICATIONS AND USAGE

NIKITA is indicated as an adjunct to diet to reduce low-density lipoprotein cholesterol (LDL-C) in:

- Adults with primary hyperlipidemia.

Pediatric use information is approved for Kowa Co Ltd's LIVALO (pitavastatin) tablets. However, due to Kowa Co Ltd's marketing exclusivity rights, this drug product is not labeled with that information.

2 DOSAGE AND ADMINISTRATION

2.1 Important Dosage and Administration Information

- Take NIKITA orally once daily with or without food at the same time each day.
- For patients that require a high-intensity statin or are unable to achieve their LDL-C goal receiving NIKITA 4 mg daily, prescribe alternative LDL-C-lowering treatment.
- Assess LDL-C when clinically appropriate, as early as 4 weeks after initiating NIKITA, and adjust the dosage if necessary.

2.2 Recommended Dosage for Adults

- The recommended dosage range of NIKITA is 2 mg to 4 mg daily.
- The maximum recommended dosage is NIKITA 4 mg once daily.

2.3 Recommended Dosage in Patients with Renal Impairment

- The recommended starting dosage for patients with moderate and severe renal impairment (estimated glomerular filtration rate 30 to 59 mL/minute/1.73 m^2and 15 to 29 mL/minute/1.73 m^2, respectively) and patients with end-stage renal disease receiving hemodialysis is NIKITA 1 mg once daily. The maximum recommended dose for these patients is NIKITA 2 mg once daily [see Use in Specific Populations (8.5)].
- There are no dosage adjustment recommendations for patients with mild renal impairment.

2.4 Dosage Modifications Due to Drug Interactions

- In patients taking erythromycin, do not exceed NIKITA 1 mg once daily [see Drug Interactions (7)] .
- In patients taking rifampin, do not exceed NIKITA 2 mg once daily [see Drug Interactions (7)] .

Pediatric use information is approved for Kowa Co Ltd's LIVALO (pitavastatin) tablets. However, due to Kowa Co Ltd's marketing exclusivity rights, this drug product is not labeled with that information.

3 DOSAGE FORMS AND STRENGTHS

Tablets:

- 1 mg: White to off-white, round, film-coated tablet, debossed with "LU" on one side and "C75" on the other side.
- 2 mg: White to off-white, round, film-coated tablet, debossed with "LU" on one side and 'C76" on the other side.
- 4 mg: White to off-white, round, film-coated tablet, debossed with "LU" on one side and "C77" on the other side.

4 CONTRAINDICATIONS

NIKITA is contraindicated in the following conditions:

- Concomitant use of cyclosporine [see Drug Interactions (7)].
- Acute liver failure or decompensated cirrhosis [see Warnings and Precautions (5.3)].
- Hypersensitivity to pitavastatin or any excipents in NIKITA. Hypersensitivity reactions including angioedema, rash, pruritus, and urticaria have been reported with NIKITA [see Adverse Reactions (6)].

5 WARNINGS AND PRECAUTIONS

5.1 Myopathy and Rhabdomyolysis

NIKITA may cause myopathy (muscle pain, tenderness, or weakness associated with elevated creatine kinase [CK]) above ten times the upper limit of normal) and rhabdomyolysis. Acute kidney injury secondary to myoglobinuria and rare fatalities have occurred as a result of rhabdomyolysis in patients treated with statins, including NIKITA.

Risk Factors for Myopathy

Risk factors for myopathy include age 65 years or greater, uncontrolled hypothyroidism, renal impairment, concomitant use of certain drugs (including other lipid-lowering therapies), and higher NIKITA dosage [see Dosage and Administration (2.2), Drug Interactions (7), and Use in Specific Populations (8.5, 8.6)]. Dosages of pitavastatin greater than 4 mg once daily were associated with an increased risk for severe myopathy in premarketing clinical studies. The maximum recommended dose of NIKITA is 4 mg once daily.

Steps to Prevent or Reduce the Risk of Myopathy and Rhabdomyolysis

NIKITA is contraindicated in patients taking cyclosporine and not recommended in patients taking gemfibrozil [see Contraindications (4) and Drug Interactions (7)]. There are NIKITA dosage restrictions for patients taking erythromycin or rifampin [see Dosage and Administration (2.4)]. The following drugs when used concomitantly with NIKITA may also increase the risk of myopathy and rhabdomyolysis: lipid-modifying dosages of niacin (>1grams/day), fibrates, and colchicine [see Drug Interactions (7)].

Discontinue NIKITA if markedly elevated CK levels occur or if myopathy is either diagnosed or suspected. Muscle symptoms and CK elevations may resolve if NIKITA is discontinued. Temporarily discontinue NIKITA in patients experiencing an acute or serious condition at high risk of developing renal failure secondary to rhabdomyolysis (e.g., sepsis; shock; severe hypovolemia; major surgery; trauma; severe metabolic, endocrine, or electrolyte disorders; or uncontrolled epilepsy).

Inform patients of the risk of myopathy and rhabdomyolysis when starting or increasing the NIKITA dosage. Instruct patients to promptly report any unexplained muscle pain, tenderness or weakness, particularly if accompanied by malaise or fever.

5.2 Immune-Mediated Necrotizing Myopathy

There have been rare reports of immune-mediated necrotizing myopathy (IMNM), an autoimmune myopathy, associated with statin use, including reports of recurrence when the same or a different statin was administered. IMNM is characterized by proximal muscle weakness and elevated serum creatine kinase that persist despite discontinuation of statin treatment; positive anti-HMG CoA reductase antibody; muscle biopsy showing necrotizing myopathy; and improvement with immunosuppressive agents. Additional neuromuscular and serologic testing may be necessary. Treatment with immunosuppressive agents may be required. Discontinue NIKITA if IMNM is suspected.

5.3 Hepatic Dysfunction

Increases in serum transaminases have been reported with NIKITA [see Adverse Reactions (6)]. In most cases, these changes appeared soon after initiation, were transient, were not accompanied by symptoms, and resolved or improved on continued therapy or after a brief interruption in therapy. There have been rare postmarketing reports of fatal and non-fatal hepatic failure in patients taking statins, including NIKITA.

Patients who consume substantial quantities of alcohol and/or have a history of liver disease may be at increased risk for hepatic injury.

Consider liver enzyme testing before the initiation of NIKITA and when clinically indicated thereafter. NIKITA is contraindicated in patients with acute liver failure or decompensated cirrhosis [see Contraindications (4)]. If serious hepatic injury with clinical symptoms and/or hyperbilirubinemia or jaundice occurs, promptly discontinue NIKITA.

5.4 Increases in HbA1c and Fasting Serum Glucose Levels

Increases in HbA1c and fasting serum glucose levels have been reported with statins, including NIKITA. Optimize lifestyle measures, including regular exercise, maintaining a healthy body weight, and making healthy food choices.

6 ADVERSE REACTIONS

The following serious adverse reactions are discussed in other sections of the labeling:

- Myopathy and Rhabdomyolysis [see Warnings and Precautions (5.1)]
- Immune-Mediated Necrotizing Myopathy [see Warning and Precautions (5.2)]
- Hepatic Dysfunction [see Warning and Precautions (5.3)]
- Increases in HbA1c and Fasting Serum Glucose Levels [see Warning and Precautions (5.4)].

6.1 Clinical Studies Experience

Because clinical studies are conducted under widely varying conditions, adverse reaction rates observed in the clinical studies of one drug cannot be directly compared to rates in the clinical studies of another drug and may not reflect the rates observed in practice.

Adverse Reactions in Adults with Primary Hyperlipidemia

In 10 controlled clinical studies and 4 subsequent open-label extension studies, 3,291 adult patients with primary hyperlipidemia were administered pitavastatin 1 mg to 4 mg daily. The mean continuous exposure of pitavastatin (1 mg to 4 mg) was 36.7 weeks (median 51.1 weeks). The mean age of the patients was 60.9 years (range; 18 years to 89 years) and 52% were females. Approximately 93% of the patients were White, 7% were Asian/Indian, 0.2% were African American and 0.3% were Hispanic and other.

In controlled clinical studies and their open-label extensions, 3.9% (1 mg), 3.3% (2 mg), and 3.7% (4 mg) of pitavastatin-treated patients were discontinued due to adverse reactions. The most common adverse reactions that led to treatment discontinuation were: elevated creatine phosphokinase (0.6% on 4 mg) and myalgia (0.5% on 4 mg).

Adverse reactions reported in > 2% of patients in controlled clinical studies and at a rate greater than or equal to placebo are shown in Table 1. These studies had treatment duration of up to 12 weeks.

Table 1: Adverse Reactions (≥ 2% and ≥ placebo) in Adults with Primary Hyperlipidemia in Studies up to 12 Weeks
Adverse Reactions | Placebo (n= 208) % | Pitavastatin 1 mg (n=309) % | Pitavastatin 2 mg (n=951) % | Pitavastatin 4 mg (n=1540) %
Myalgia | 1.4 | 1.9 | 2.8 | 3.1
Constipation | 1.9 | 3.6 | 1.5 | 2.2
Diarrhea | 1.9 | 2.6 | 1.5 | 1.9
Back Pain | 2.9 | 3.9 | 1.8 | 1.4
Pain in extremity | 1.9 | 2.3 | 0.6 | 0.9

Other adverse reactions reported from clinical studies were arthralgia, headache, influenza, and nasopharyngitis.

Hypersensitivity reactions including rash, pruritus, and urticaria have been reported with pitavastatin.

The following laboratory abnormalities have been reported: elevated creatine phosphokinase, transaminases, alkaline phosphatase, bilirubin, and glucose.

Adverse Reactions in Adult HIV-Infected Patients with Dyslipidemia

In a double-blind, randomized, controlled, 52-week trial, 252 HIV-infected patients with dyslipidemia were treated with either pitavastatin 4 mg once daily (n=126) or another statin (n=126). All patients were taking antiretroviral therapy (excluding darunavir) and had HIV-1 RNA less than 200 copies/mL and CD4 count greater than 200 cell/µL for at least 3 months prior to randomization. The safety profile of pitavastatin was generally consistent with that observed in the clinical trials described above. One patient (0.8%) treated with pitavastatin had a peak creatine phosphokinase value exceeding 10 times the upper limit of normal (ULN), which resolved spontaneously. Four patients (3%) treated with pitavastatin had at least one ALT value exceeding 3 times but less than 5 times the ULN, none of which led to drug discontinuation. Virologic failure was reported for four patients (3%) treated with pitavastatin, defined as a confirmed measurement of HIV-1 RNA exceeding 200 copies/mL that was also more than a 2-fold increase from baseline.

Pediatric use information is approved for Kowa Co Ltd's LIVALO (pitavastatin) tablets. However, due to Kowa Co Ltd's marketing exclusivity rights, this drug product is not labeled with that information.

6.2 Postmarketing Experience

The following adverse reactions have been identified during postapproval use of pitavastatin. Because these reactions are reported voluntarily from a population of uncertain size, it is not always possible to reliably estimate their frequency or establish a causal relationship to drug exposure.

Gastrointestinal disorders: abdominal discomfort, abdominal pain, dyspepsia, nausea

General disorders: asthenia, fatigue, malaise, dizziness

Hepatobiliary disorders: hepatitis, jaundice, fatal and non-fatal hepatic failure

Immune system disorders: angioedema, immune-mediated necrotizing myopathy associated with statin use.

Metabolism and nutrition disorders: increases in HbA1c, fasting serum glucose levels

Musculoskeletal and connective tissue disorders: muscle spasms, myopathy, rhabdomyolysis

Nervous system disorders: hypoesthesia, peripheral neuropathy

Psychiatric disorders: insomnia, depression. Rare reports of cognitive impairment (e.g., memory loss, forgetfulness, amnesia, memory impairment, confusion) associated with statin use. Cognitive impairment was generally nonserious, and reversible upon statin discontinuation, with variable times to symptom onset (1 day to years) and symptom resolution (median of 3 weeks).

Reproductive system and breast disorders: erectile dysfunction

Respiratory, thoracic and mediastinal disorders: interstitial lung disease

Skin and subcutaneous tissue disorders: lichen planus

7 DRUG INTERACTIONS

Table 2 includes a list of drugs that increase the risk of myopathy and rhabdomyolysis when administered concomitantly with NIKITA and instructions for preventing or managing drug interactions [see Warnings and Precautions (5.1), Clinical Pharmacology (12.3)].

Table 2: Drug Interactions that Increase the Risk of Myopathy and Rhabdomyolysis with NIKITA
Cyclosporine
Clinical Impact: | Cyclosporine significantly increases pitavastatin exposure and increases the risk of myopathy and rhabdomyolysis.
Intervention: | Concomitant use of cyclosporine with NIKITA is contraindicated [see Contraindications (4)].
Gemfibrozil
Clinical Impact: | Gemfibrozil may cause myopathy when given alone. The risk of myopathy and rhabdomyolysis is increased with concomitant use of gemfibrozil with statins, including NIKITA.
Intervention: | Avoid concomitant use of gemfibrozil with NIKITA.
Erythromycin
Clinical Impact: | Erythromycin significantly increases pitavastatin exposure and increases the risk of myopathy and rhabdomyolysis.
Intervention: | In patients taking erythromycin, do not exceed NIKITA 1 mg once daily [see Dosage and Administration (2.4)].
Rifampin
Clinical Impact: | Rifampin significantly increases peak pitavastatin exposure and increases the risk of myopathy and rhabdomyolysis.
Intervention: | In patients taking rifampin, do not exceed NIKITA 2 mg once daily [see Dosage and Administration (2.4)].
Fibrates
Clinical Impact: | Fibrates may cause myopathy when given alone. The risk of myopathy and rhabdomyolysis is increased with concomitant use of fibrates with statins, including NIKITA.
Intervention: | Consider if the benefit of using fibrates concomitantly with NIKITA outweighs the increased risk of myopathy and rhabdomyolysis.
Niacin
Clinical Impact: | The risk of myopathy and rhabdomyolysis may be increased with concomitant use of lipid modifying doses (≥1 g/day) of niacin with NIKITA.
Intervention: | Consider if the benefit of using lipid-modifying doses (> 1 g/day) of niacin concomitantly with NIKITA outweighs the increased risk of myopathy and rhabdomyolysis.
Colchicine
Clinical Impact: | Cases of myopathy and rhabdomyolysis have been reported with concomitant use of colchicine with statins, including NIKITA.
Intervention: | Consider the risk/benefit of concomitant use of colchicine with NIKITA.

8 USE IN SPECIFIC POPULATIONS

8.1 Pregnancy

Risk Summary

Discontinue NIKITA when pregnancy is recognized. Alternatively, consider the ongoing therapeutic needs of the individual patient.

NIKITA decreases synthesis of cholesterol and possibly other biologically active substances derived from cholesterol; therefore, NIKITA may cause fetal harm when administered to pregnant patients based on the mechanism of action [see Clinical Pharmacology (12.1)]. In addition, treatment of hyperlipidemia is not generally necessary during pregnancy. Atherosclerosis is a chronic process and the discontinuation of lipid-lowering drugs during pregnancy should have little impact on the outcome of long-term therapy of primary hyperlipidemia for most patients.

Available data from case series and prospective and retrospective observational cohort studies over decades of use with statins in pregnant women have not identified a drug-associated risk of major congenital malformations. Published data from prospective and retrospective observational cohort studies with statin use in pregnant women are insufficient to determine if there is a drug associated risk of miscarriage (see Data).

In animal reproduction studies, no embryo-fetal toxicity or congenital malformations were observed in pregnant rats and rabbits orally administered pitavastatin during the period of organogenesis at doses which were 22 and 4 times, respectively, the human exposure at the maximum recommended human dosage (MRHD) of 4 mg, based on AUC [see Data].

The estimated background risk of major birth defects and miscarriage for the indicated population is unknown. In the U.S. general population, the estimated background risk of major birth defects and miscarriage in clinically recognized pregnancies is 2 to 4% and 15 to 20%, respectively.

Data

Human Data:

A Medicaid cohort linkage study of 1152 statin-exposed pregnant women compared to 886,996 controls did not find a significant teratogenic effect from maternal use of statins in the first trimester of pregnancy, after adjusting for potential confounders – including maternal age, diabetes mellitus, hypertension, obesity, and alcohol and tobacco use – using propensity score-based methods. The relative risk of congenital malformations between the group with statin use and the group with no statin use in the first trimester was 1.07 (95% confidence interval 0.85 to 1.37) after controlling for confounders, particularly pre-existing diabetes mellitus. There were also no statistically significant increases in any of the organ-specific malformations assessed after accounting for confounders. In the majority of pregnancies, statin treatment was initiated prior to pregnancy and was discontinued at some point in the first trimester when pregnancy was identified. Study limitations include reliance on physician coding to define the presence of a malformation, lack of control for certain confounders such as body mass index, use of prescription dispensing as verification for the use of a statin, and lack of information on non-live births.

Animal Data:

Embryo-fetal developmental studies were conducted in pregnant rats administered 3, 10, 30 mg/kg/day pitavastatin by oral gavage during organogenesis (gestation days 7-17). No adverse effects were observed at 3 mg/kg/day, systemic exposures 22 times human systemic exposure at 4 mg/day based on AUC.

Embryo-fetal developmental studies were conducted in pregnant rabbits administered 0.1, 0.3, 1 mg/kg/day pitavastatin by oral gavage during the period of fetal organogenesis (gestation days 6-18). Maternal toxicity consisting of reduced body weight and abortion was observed at all doses tested (4 times human systemic exposure at 4 mg/day based on AUC).

In perinatal/postnatal studies in pregnant rats given oral gavage doses of pitavastatin at 0.1, 0.3, 1, 3, 10, 30 mg/kg/day from organogenesis through weaning (gestation day 17 to lactation day 21), maternal toxicity consisting of mortality at ≥0.3 mg/kg/day and impaired lactation at all doses contributed to the decreased survival of neonates in all dose groups (0.1 mg/kg/day represents approximately 1 time human systemic exposure at 4 mg/day dose based on AUC).

Reproductive toxicity studies have shown that pitavastatin crosses the placenta in rats and is found in fetal tissues at ≤36% of maternal plasma concentrations following a single dose of 1 mg/kg/day during gestation (at the end of organogenesis).

8.2 Lactation

Risk Summary

There is no available information about the prescence of pitavastatin in human or animal milk, the effects of the drug on the breastfed infant, or the effects of the drug on milk production. However, it has been shown that another drug in this class passes into human milk. Statins, including NIKITA, decrease cholesterol synthesis and possibly the synthesis of other biologically active substances derived from cholesterol and may cause harm to the breastfed infant.

Because of the potential for serious adverse reactions in a breastfed infant, based upon the mechanism of action, advise patients that breastfeeding is not recommended during treatment with NIKITA. [see Use in Specific Populations (8.1), Clinical Pharmacology (12.1)]

8.4 Pediatric Use

The safety and effectiveness of NIKITA in pediatric patients have not been established.

Pediatric use information is approved for Kowa Co Ltd's LIVALO (pitavastatin) tablets. However, due to Kowa Co Ltd's marketing exclusivity rights, this drug product is not labeled with that information.

8.5 Geriatric Use

In controlled clinical studies, 1,209 (43%) patients were 65 years and older. No overall differences in safety or effectiveness were observed between these patients and younger patients.

Advanced age (≥65 years) is a risk factor for NIKITA-associated myopathy and rhabdomyolysis. Dose selection for a geriatric patient should be cautious, reognizing the greater frequency of decreased hepatic, renal, or cardiac function, and of concomitant disease or other drug therapy and the higher risk of myopathy. Monitor geriatric patients receiving NIKITA for the increased risk of myopathy [see Warnings and Precautions (5.1)].

8.6 Renal Impairment

Renal impairment is a risk factor for myopathy and rhabdomyolysis. Monitor all patients with renal impairment for development of myopathy. Due to the risk of myopathy, a dosage modification of NIKITA is recommended for patients with moderate and severe renal impairment (estimated glomerular filtration rate 30 to 59 mL/min/1.73 m^2and 15 to 29 mL/min/1.73 m^2, respectively), as well as end-stage renal disease receiving hemodialysis. [see Dosage and Administration (2.3), Warnings and Precautions (5.1), Clinical Pharmacology (12.3)].

8.7 Hepatic Impairment

NIKITA is contraindicated in patients with active liver failure or decompensated cirrhosis [see Contraindications (4), Warnings and Precautions (5.3)].

10 OVERDOSAGE

No specific treatment for NIKITA overdose is known. Contact Poison Control (1-800-222-1222) for latest recommendations. Hemodialysis is unlikely to be of benefit due to high protein binding ratio of NIKITA.

11 DESCRIPTION

NIKITA (pitavastatin) tablets for oral use is an HMG-CoA reductase inhibitor.

The chemical name for pitavastatin is Sodium (3R, 5S, E)-7-(2-cyclopropyl-4-(4-fluorophenyl)-quinolin-3-yl)-3, 5-dihydroxyhept-6-enoate. The structural formula is:

The empirical formula for pitavastatin is C25H23FNO4Na and the molecular weight is 443.15. Pitavastatin occurs as white to pale yellow powder. It is slightly soluble in N, N-Dimethylformamide. Pitavastatin is slightly hygroscopic in nature and slightly unstable in light.

Each film-coated tablet of NIKITATM contains 1.052 mg, 2.103 mg, or 4.206 mg of pitavastatin sodium, which is equivalent to 1 mg, 2 mg, or 4 mg, respectively of pitavastatin, and the following inactive ingredients: hypromellose, lactose monohydrate, low substituted hydroxypropylcellulose, magnesium stearate and sodium bicarbonate and film coating containing the following inactive ingredients: colloidal anhydrous silica, hypromellose, titanium dioxide and triethyl citrate.

12 CLINICAL PHARMACOLOGY

12.1 Mechanism of Action

Pitavastatin is an inhibitor of 3-hydroxy-3-methylglutaryl-coenzyme A (HMG-CoA) reductase, the enzyme that catalyzes the conversion of HMG-CoA to mevalonate, a rate-limiting step in the biosynthetic pathway for cholesterol. As a result, the expression of LDL-receptors followed by the uptake of LDL from blood to liver is accelerated and then the plasma TC decreases. Sustained inhibition of cholesterol synthesis in the liver also decreases levels of very low density lipoproteins.

12.2 Pharmacodynamics

Cardiac Electrophysiology

In a randomized, double-blind, placebo-controlled, 4-way parallel, active-comparator study with moxifloxacin in 174 healthy participants, pitavastatin was not associated with clinically meaningful prolongation of the QTc interval or heart rate at daily doses up to 16 mg (4 times the recommended maximum dose of 4 mg daily).

12.3 Pharmacokinetics

Absorption

Pitavastatin peak plasma concentrations are achieved about 1 hour after oral administration. Both Cmax and AUC0 to inf increased in an approximately dose-proportional manner for single pitavastatin doses from 1 mg to 24 mg once daily. The absolute bioavailability of pitavastatin oral solution is 51%. The Cmax and AUC of pitavastatin did not differ following evening or morning drug administration. In healthy volunteers receiving 4 mg pitavastatin, the percent change from baseline for LDL-C following evening dosing was slightly greater than that following morning dosing. Pitavastatin was absorbed in the small intestine but very little in the colon.

Effect of Food:

Administration of pitavastatin with a high fat meal (50% fat content) decreases pitavastatin Cmax by 43% but does not significantly reduce pitavastatin AUC.

Distribution

Pitavastatin is more than 99% protein bound in human plasma, mainly to albumin and alpha 1-acid glycoprotein, and the mean volume of distribution is approximately 148 L.

Elimination

Metabolism

The principal route of pitavastatin metabolism is glucuronidation via liver uridine 5'-diphosphate glucuronosyltransferase (UGT) with subsequent formation of pitavastatin lactone. There is only minimal metabolism by the cytochrome P450 system. Pitavastatin is marginally metabolized by CYP2C9 and to a lesser extent by CYP2C8. The major metabolite in human plasma is the lactone, which is formed via an ester-type pitavastatin glucuronide conjugate by UGTs (UGT1A3 and UGT2B7).

Excretion

A mean of 15% of radioactivity of orally administered, single 32 mg ^14C-labeled pitavastatin dose was excreted in urine, whereas a mean of 79% of the dose was excreted in feces within 7 days. The mean plasma elimination half-life is approximately 12 hours.

Specific Populations

Geriatric Patients

In a pharmacokinetic study which compared healthy young and geriatric (≥65 years) volunteers, pitavastatin Cmax and AUC were 10 and 30% higher, respectively, in the geriatric patients [see Use in Specific Populations (8.4)]

Pediatric use information is approved for Kowa Co Ltd's LIVALO (pitavastatin) tablets. However, due to Kowa Co Ltd's marketing exclusivity rights, this drug product is not labeled with that information.

Male and Female Patients

In a pharmacokinetic study, which compared healthy male and female volunteers, pitavastatin Cmax and AUC were 60 and 54% higher, respectively in females.

Racial or Ethnic Groups

In pharmacokinetic studies pitavastatin Cmax and AUC were 21 and 5% lower, respectively in Black or African American healthy volunteers compared with those of White healthy volunteers. In pharmacokinetic comparison between White volunteers and Japanese volunteers, there were no significant differences in Cmax and AUC.

Patients with Renal Impairment

In adult patients with moderate renal impairment (estimated glomerular filtration rate of 30 to 59 mL/min/1.73 m^2) and end stage renal disease receiving hemodialysis, pitavastatin AUC0 to inf is 102% and 86% higher than those of healthy volunteers, respectively, while pitavastatin Cmax is 60% and 40% higher than those of healthy volunteers, respectively. Patients received hemodialysis immediately before pitavastatin dosing and did not undergo hemodialysis during the pharmacokinetic study. Hemodialysis patients have 33% and 36% increases in the mean unbound fraction of pitavastatin as compared to healthy volunteers and patients with moderate renal impairment, respectively [see Use in Specific Populations (8.5)].

In another pharmacokinetic study, adult patients with severe renal impairment (estimated glomerular filtration rate 15 to 29 mL/min/1.73 m^2) not receiving hemodialysis were administered a single dose of pitavastatin 4 mg. The AUC0 to inf and the Cmax were 36% and 18% higher, respectively, compared with those of healthy volunteers. For both patients with severe renal impairment and healthy volunteers, the mean percentage of protein-unbound pitavastatin was approximately 0.6% [see Use in Specific Populations (8.5)].

The effect of mild renal impairment on pitavastatin exposure has not been studied.

Patients with Hepatic Impairment

The disposition of pitavastatin was compared in healthy volunteers and patients with various degrees of hepatic impairment. Pitavastatin Cmax and AUCinf in patients with moderate hepatic impairment (Child-Pugh B disease) was 2.7-fold and 3.8-fold higher, respectively as compared to healthy volunteers. In patients with mild hepatic impairment (Child-Pugh A disease), pitavastatin Cmax and AUCinf were 30% and 60% higher as compared to healthy volunteers. Mean pitavastatin half-life for moderate hepatic impairment, mild hepatic impairment, and healthy volunteers were 15, 10, and 8 hours, respectively [see Contraindications (4), Warnings and Precautions (5.3)].

Drug Interaction Studies

Warfarin

The steady-state pharmacodynamics (international normalized ratio [INR] and prothrombin time [PT]) and pharmacokinetics of warfarin in healthy volunteers were unaffected by the coadministration of pitavastatin 4 mg daily.

Table 3 presents the effect of coadministered drugs on pitavastatin systemic exposure:

Table 3: Effect of Coadministered Drugs on Pitavastatin Systemic Exposure
Coadministered drug | Dosage regimen | Change in AUC* | Change in Cmax *
Cyclosporine | Pitavastatin 2 mg QD for 6 days + cyclosporine 2 mg/kg on Day 6 | ↑ 4.6 fold † | ↑ 6.6 fold †
Erythromycin | Pitavastatin 4 mg single dose on Day 4 + erythromycin 500 mg 4 times daily for 6 days | ↑ 2.8 fold † | ↑ 3.6 fold †
Rifampin | Pitavastatin 4 mg QD + rifampin 600 mg QD for 5 days | ↑ 29% | ↑ 2.0 fold †
Atazanavir | Pitavastatin 4 mg QD + atazanavir 300 mg daily for 5 days | ↑ 31% | ↑ 60%
Darunavir/Ritonavir | Pitavastatin 4mg QD on Days 1 to 5 and 12 to 16 + darunavir/ritonavir 800mg/100 mg QD on Days 6 to 16 | ↓ 26% | ↓ 4%
Lopinavir/Ritonavir | Pitavastatin 4 mg QD on Days 1 to 5 and 20 to 24 + lopinavir/ritonavir 400 mg/100 mg BID on Days 9 to 24 | ↓ 20% | ↓4 %
Gemfibrozil | Pitavastatin 4 mg QD + gemfibrozil 600 mg BID for 7 days | ↑ 45% | ↑ 31%
Fenofibrate | Pitavastatin 4 mg QD + fenofibrate 160 mg QD for 7 days | ↑18% | ↑ 11%
Ezetimibe | Pitavastatin 2 mg QD + ezetimibe 10 mg for 7 days | ↓ 2% | ↓0.2%
Enalapril | Pitavastatin 4 mg QD + enalapril 20 mg daily for 5 days | ↑ 6% | ↓ 7%
Digoxin | Pitavastatin 4 mg QD + digoxin 0.25 mg for 7 days | ↑ 4% | ↓ 9%
Diltiazem LA | Pitavastatin 4 mg QD on Days 1 to 5 and 11 to 15 and diltiazem LA 240 mg on Days 6 to 15 | ↑10% | ↑15%
Grapefruit Juice | Pitavastatin 2 mg single dose on Day 3 + grapefruit juice for 4 days | ↑ 15% | ↓ 12%
Itraconazole | Pitavastatin 4 mg single dose on Day 4 + itraconazole 200 mg daily for 5 days | ↓ 23% | ↓ 22%

*Data presented as x-fold change represent the ratio between coadministration and pitavastatin alone (i.e., 1-fold = no change). Data presented as % change represent % difference relative to pitavastatin alone (i.e., 0% = no change).

† Considered clinically significant [see Dosage and Administration (2.4), Drug Interactions (7)] BID = twice daily; QD = once daily; LA = Long Acting

Table 4 presents the effect of pitavastatin coadministration on systemic exposure of other drugs:

Table 4: Effect of Pitavastatin Coadministration on Systemic Exposure to Other Drugs
Coadministered drug | Dosage regimen |  | Change in AUC* | Change in Cmax *
Atazanavir | Pitavastatin 4 mg QD + atazanavir 300 mg daily for 5 days |  | ↑ 6% | ↑ 13%
Darunavir | Pitavastatin 4mg QD on Days 1 to 5 and 12 to 16 + darunavir/ritonavir 800mg/100 mg QD on Days 6 to 16 |  | ↑ 3% | ↑ 6%
Lopinavir | Pitavastatin 4 mg QD on Days 1 to 5 and 20 to 24 + lopinavir/ritonavir 400 mg/100 mg BID on Days 9 to 24 |  | ↓ 9% | ↓ 7%
Ritonavir | Pitavastatin 4 mg QD on Days 1 to 5 and 20 to 24 + lopinavir/ritonavir 400 mg/100 mg BID on Days 9 to 24 |  | ↓ 11% | ↓ 11%
Ritonavir | Pitavastatin 4mg QD on Days 1 to 5 and 12 to 16 + darunavir/ritonavir 800mg/100 mg QD on Days 6 to 16 |  | ↑ 8% | ↑ 2%
Enalapril | Pitavastatin 4 mg QD + enalapril 20 mg daily for 5 days | Enalapril | ↑ 12% | ↑ 12%
Enalapril | Pitavastatin 4 mg QD + enalapril 20 mg daily for 5 days | Enalaprilat | ↓ 1% | ↓ 1%
Warfarin | Individualized maintenance dose of warfarin (2 to 7 mg) for 8 days + pitavastatin 4 mg QD for 9 days | R-warfarin | ↑ 7% | ↑ 3%
Warfarin | Individualized maintenance dose of warfarin (2 to 7 mg) for 8 days + pitavastatin 4 mg QD for 9 days | S-warfarin | ↑ 6% | ↑ 3%
Ezetimibe | Pitavastatin 2 mg QD + ezetimibe 10 mg for 7 days |  | ↑ 9% | ↑ 2%
Digoxin | Pitavastatin 4 mg QD + digoxin 0.25 mg for 7 days |  | ↓ 3% | ↓ 4%
Diltiazem LA | Pitavastatin 4 mg QD on Days 1 to 5 and 11 to 15 and diltiazem LA 240 mg on Days 6 to 15 |  | ↓ 2% | ↓ 7%
Rifampin | Pitavastatin 4 mg QD + rifampin 600 mg QD for 5 days |  | ↓ 15% | ↓ 18%

*Data presented as % change represent % difference relative to the investigated drug alone (i.e., 0% = no change).

BID = twice daily; QD = once daily; LA = Long Acting

13 NONCLINICAL TOXICOLOGY

13.1 Carcinogenesis, Mutagenesis, Impairment of Fertility

In a 92-week carcinogenicity study in mice given pitavastatin, at the maximum tolerated dose of 75 mg/kg/day with systemic maximum exposures (AUC) 26 times the clinical maximum exposure at 4 mg daily, there was an absence of drug-related tumors.

In a 92-week carcinogenicity study in rats given pitavastatin at 1, 5, 25 mg/kg/day by oral gavage there was a significant increase in the incidence of thyroid follicular cell tumors at 25 mg/kg/day, which represents 295 times human systemic exposures based on AUC at the 4 mg daily maximum human dose.

In a 26-week transgenic mouse (Tg rasH2) carcinogenicity study where animals were given pitavastatin at 30, 75, and 150 mg/kg/day by oral gavage, no clinically significant tumors were observed.

Pitavastatin was not mutagenic in the Ames test with Salmonella typhimurium and Escherichia coli with and without metabolic activation, the micronucleus test following a single administration in mice and multiple administrations in rats, the unscheduled DNA synthesis test in rats, and a Comet assay in mice. In the chromosomal aberration test, clastogenicity was observed at the highest doses tested, which also elicited high levels of cytotoxicity.

Pitavastatin had no adverse effects on male and female rat fertility at oral doses of 10 and 30 mg/kg/day, respectively, at systemic exposures 56- and 354-times clinical exposure at 4 mg daily based on AUC.

Pitavastatin treatment in rabbits resulted in mortality in males and females given 1 mg/kg/day (30-times clinical systemic exposure at 4 mg daily based on AUC) and higher during a fertility study. Although the cause of death was not determined, rabbits had gross signs of renal toxicity (kidneys whitened) indicative of possible ischemia. Lower doses (15-times human systemic exposure) did not show significant toxicity in adult males and females. However, decreased implantations, increased resorptions, and decreased viability of fetuses were observed.

14 CLINICAL STUDIES

Primary Hyperlipidemia in Adults

Study with Atorvastatin (Study 301)

Pitvastatin was compared with atorvastatin calcium tablets (referred to as atorvastatin) in a randomized, multicenter, double-blind, double-dummy, active-controlled, non-inferiority study of 817 adult patients with primary hyperlipidemia or mixed dyslipidemia. Patients entered a 6- to 8-week wash-out/dietary lead-in period and then were randomized to a 12-week treatment with either pitavastatin or atorvastatin (Table 5). Non-inferiority of pitavastatin to a given dose of atorvastatin was considered to be demonstrated if the lower bound of the 95% CI for the mean treatment difference was greater than -6% for the mean percent change in LDL-C.

Lipid results are shown in Table 5. For the percent change from baseline to endpoint in LDL-C, pitavastatin was non-inferior to atorvastatin for the two pairwise comparisons: pitavastatin 2 mg vs. atorvastatin 10 mg and pitavastatin 4 mg vs. atorvastatin 20 mg. Mean treatment differences (95% CI) were 0% (-3%, 3%) and 1% (-2%, 4%), respectively.

Table 5: Lipid Response by Dose of Pitavastatin and Atorvastatin in Adult Patients with Primary Hyperlipidemia or Mixed Dyslipidemia in Study 301 (Mean % Change from Baseline at Week 12)
Treatment | N | LDL-C | Apo-B | TC | TG | HDL-C | non-HDL-C
Pitavastatin 2 mg daily | 315 | -38 | -30 | -28 | -14 | 4 | -35
Pitavastatin 4 mg daily | 298 | -45 | -35 | -32 | -19 | 5 | -41
Atorvastatin 10 mg daily | 102 | -38 | -29 | -28 | -18 | 3 | -35
Atorvastatin 20 mg daily | 102 | -44 | -36 | -33 | -22 | 2 | -41

Study with Simvastatin (Study 302)

Pitavastatin was compared with simvastatin tablets (referred to as simvastatin) in a randomized, multicenter, double-blind, double-dummy, active-controlled, non-inferiority study of 843 adult patients with primary hyperlipidemia or mixed dyslipidemia. Patients entered a 6- to 8-week wash-out/dietary lead-in period and then were randomized to a 12 week treatment with either pitavastatin or simvastatin (Table 6). Non-inferiority of pitavastatin to a given dose of simvastatin was considered to be demonstrated if the lower bound of the 95% CI for the mean treatment difference was greater than -6% for the mean percent change in LDL-C.

Lipid results are shown in Table 6. For the percent change from baseline to endpoint in LDL-C, pitavastatin was non-inferior to simvastatin for the two pairwise comparisons: pitavastatin 2 mg vs. simvastatin 20 mg and pitavastatin 4 mg vs. simvastatin 40 mg. Mean treatment differences (95% CI) were 4% (1%, 7%) and 1% (-2%, 4%), respectively.

Table 6: Lipid Response by Dose of Pitavastatin and Simvastatin in Adult Patients with Primary Hyperlipidemiaor Mixed Dyslipidemia in Study 302 (Mean % Change from Baseline at Week 12)
Treatment | N | LDL-C | Apo-B | TC | TG | HDL-C | non-HDL-C
Pitavastatin 2 mg daily | 307 | -39 | -30 | -28 | -16 | 6 | -36
Pitavastatin 4 mg daily | 319 | -44 | -35 | -32 | -17 | 6 | -41
Simvastatin 20 mg daily | 107 | -35 | -27 | -25 | -16 | 6 | -32
Simvastatin 40 mg daily | 110 | -43 | -34 | -31 | -16 | 7 | -39

Study with Pravastatin in Geriatric Patients (Study 306)

Pitavastatin was compared with pravastatin sodium tablets (referred to as pravastatin) in a randomized, multicenter, double-blind, double-dummy, parallel group, active-controlled non-inferiority study of 942 geriatric patients (≥65 years) with primary hyperlipidemia or mixed dyslipidemia. Patients entered a 6- to 8-week wash-out/dietary lead-in period, and then were randomized to a once daily dose of pitavastatin or pravastatin for 12 weeks (Table 7). Non-inferiority of pitavastatin to a given dose of pravastatin was assumed if the lower bound of the 95% CI for the treatment difference was greater than -6% for the mean percent change in LDL-C.

Lipid results are shown in Table 7. Pitavastatin significantly reduced LDL-C compared to pravastatin as demonstrated by the following pairwise dose comparisons: pitavastatin 1 mg vs. pravastatin 10 mg, pitavastatin 2 mg vs. pravastatin 20 mg and pitavastatin 4 mg vs. pravastatin 40 mg. Mean treatment differences (95% CI) were 9% (6%, 12%), 10% (7%, 13%) and 10% (7%, 13%), respectively.

Table 7: Lipid Response by Dose of Pitavastatin and Pravastatin in Geriatric Patients with Primary Hyperlipidemia or Mixed Dyslipidemia in Study 306 (Mean % Change from Baseline at Week 12)
Treatment | N | LDL-C | Apo-B | TC | TG | HDL-C | non-HDL-C
Pitavastatin 1 mg daily | 207 | -31 | -25 | -22 | -13 | 1 | -29
Pitavastatin 2 mg daily | 224 | -39 | -31 | -27 | -15 | 2 | -36
Pitavastatin 4 mg daily | 210 | -44 | -37 | -31 | -22 | 4 | -41
Pravastatin 10 mg daily | 103 | -22 | -17 | -15 | -5 | 0 | -20
Pravastatin 20 mg daily | 96 | -29 | -22 | -21 | -11 | -1 | -27
Pravastatin 40 mg daily | 102 | -34 | -28 | -24 | -15 | 1 | -32

Study with Simvastatin in Patients with ≥2 Risk Factors for Coronary Heart Disease (Study 304)

Pitavastatin was compared with simvastatin tablets (referred to as simvastatin) in a randomized, multicenter, double-blind, double-dummy, active-controlled, non-inferiority study of 351 adult patients with primary hyperlipidemia or mixed dyslipidemia with ≥2 risk factors for coronary heart disease. After a 6- to 8-week wash-out/dietary lead-in period, patients were randomized to a 12-week treatment with either pitavastatin or simvastatin (Table 8). Non-inferiority of pitavastatin to simvastatin was considered to be demonstrated if the lower bound of the 95% CI for the mean treatment difference was greater than -6% for the mean percent change in LDL-C.

Lipid results are shown in Table 8. Pitavastatin 4 mg was non-inferior to simvastatin 40 mg for percent change from baseline to endpoint in LDL-C. The mean treatment difference (95% CI) was 0% (-2%, 3%).

Table 8. Lipid Response by Dose of Pitavastatin and Simvastatin in Adult Patients with Primary Hyperlipidemia or Mixed Dyslipidemia with ≥2Risk Factors for Coronary Heart Disease in Study 304 (Mean % Change from Baseline at Week 12)
Treatment | N | LDL-C | Apo-B | TC | TG | HDL-C | non-HDL-C
Pitavastatin 4 mg daily | 233 | -44 | -34 | -31 | -20 | 7 | -40
Simvastatin 40 mg daily | 118 | -44 | -34 | -31 | -15 | 5 | -39

Study with Atorvastatin in Patients with Type 2 Diabetes Mellitus (Study 305)

Pitavastatin was compared with atorvastatin calcium tablets (referred to as atorvastatin) in a randomized, multicenter, double-blind, double-dummy, parallel group, active-controlled, non-inferiority study of 410 adult patients with type 2 diabetes mellitus and mixed dyslipidemia. Patients entered a 6- to 8-week washout/dietary lead-in period and were randomized to a once daily dose of pitavastatin or atorvastatin for 12 weeks. Non-inferiority of pitavastatin was considered to be demonstrated if the lower bound of the 95% CI for the mean treatment difference was greater than -6% for the mean percent change in LDL-C.

Lipid results are shown in Table 9. The treatment difference (95% CI) for LDL-C percent change from baseline was -2% (-6.2%, 1.5%). The two treatment groups were not statistically different on LDL-C. However, the lower limit of the CI was -6.2%, slightly exceeding the -6% non-inferiority limit. The study failed to demonstrate that pitavastatin was not significantly different than atorvastatin in lowering LDL-C in patients with type 2 diabetes mellitus and mixed dyslipidemia.

Table 9: Lipid Response by Dose of Pitavastatin and Atorvastatin in Adult Patients with Type 2 Diabetes Mellitus and Mixed Dyslipidemia in Study 305 (Mean % Change from Baseline at Week 12)
Treatment | N | LDL-C | Apo-B | TC | TG | HDL-C | non-HDL-C
Pitavastatin 4 mg daily | 274 | -41 | -32 | -28 | -20 | 7 | -36
Atorvastatin 20 mg daily | 136 | -43 | -34 | -32 | -27 | 8 | -40

The treatment differences in efficacy in LDL-C change from baseline between pitavastatin and active controls (i.e., atorvastatin, simvastatin, or pravastatin) in the active-controlled studies described above are summarized in Figure 1.

Figure 1: Treatment Difference in Adjusted Mean Percent Change in LDL-C between Pitavastatin and the Comparator (Atorvastatin, Simvastatin, or Pravastatin)

NL=non-inferiority limit.

Pediatric use information is approved for Kowa Co Ltd's LIVALO (pitavastatin) tablets. However, due to Kowa Co Ltd's marketing exclusivity rights, this drug product is not labeled with that information.

16 HOW SUPPLIED/STORAGE AND HANDLING

NIKITA tablets are available as follows:

Strength | Description | Bottle Size | NDC
1 mg Tablet | White to off-white round film-coated tablets debossed with "LU" on one side and "C75" on the other side | 30 tablets | 68180-742-06
1 mg Tablet | White to off-white round film-coated tablets debossed with "LU" on one side and "C75" on the other side | 60 tablets | 68180-742-07
1 mg Tablet | White to off-white round film-coated tablets debossed with "LU" on one side and "C75" on the other side | 90 tablets | 68180-742-09
2 mg Tablet | White to off-white round film-coated tablets debossed with "LU" on one side and "C76" on the other side | 30 tablets | 68180-743-06
2 mg Tablet | White to off-white round film-coated tablets debossed with "LU" on one side and "C76" on the other side | 60 tablets | 68180-743-07
2 mg Tablet | White to off-white round film-coated tablets debossed with "LU" on one side and "C76" on the other side | 90 tablets | 68180-743-09
4 mg Tablet | White to off-white round film-coated tablets debossed with "LU" on one side and "C77" on the other side | 30 tablets | 68180-744-06
4 mg Tablet | White to off-white round film-coated tablets debossed with "LU" on one side and "C77" on the other side | 60 tablets | 68180-744-07
4 mg Tablet | White to off-white round film-coated tablets debossed with "LU" on one side and "C77" on the other side | 90 tablets | 68180-744-09

Store at 25°C (77°F); excursions permitted to 15° to 30°C (59° to 86°F) [see USP Controlled Room Temperature]. Protect from light.

17 PATIENT COUNSELING INFORMATION

Myopathy and Rhabdomyolysis

Advise patients that NIKITA may cause myopathy and rhabdomyolysis. Inform patients that the risk is increased when taking certain types of medication and they should discuss all medication, both prescription and over the counter, with their healthcare provider. Instruct patients to promptly report any unexplained muscle pain, tenderness or weakness particularly if accompanied by malaise or fever [see Warnings and Precautions (5.1)].

Hepatic Dysfunction

Inform patients that NIKITA may cause liver enzyme elevations and possibly liver failure. Advise patients to promptly report fatigue, anorexia, right upper abdominal discomfort, dark urine or jaundice [see Warnings and Precautions (5.3)].

Increases in HbA1c and Fasting Serum Glucose Levels

Inform patients that increases in HbA1c and fasting serum glucose levels may occur with NIKITA. Encourage patients to optimize lifestyle measures, including regular exercise, maintaining a healthy body weight, and making healthy food choices [see Warnings and Precautions (5.4)].

Pregnancy

Advise pregnant patients and patients who become pregnant of the potential risk to a fetus. Advise patients to inform their healthcare provider of a known or suspected pregnancy to discuss if NIKITA should be discontinued [see Use in Specific Populations (8.1)].

Lactation

Advise patients that breastfeeding is not recommended during treatment with NIKITA [see Use in Specific Populations (8.2)].

Manufactured for:

Lupin Pharmaceuticals, Inc.

Baltimore, Maryland 21202

United States

Manufactured by:

Lupin Limited

Nagpur 441 108

INDIA

July 2023 ID#: XXXXXX

PACKAGE LABEL.PRINCIPAL DISPLAY PANEL

NIKITA (pitavastatin) tablets, 1 mg

Bottle of 30 Tablets

NDC 68180-742-06

Rx Only

NIKITA (pitavastatin) tablets, 2 mg

Bottle of 30 Tablets

NDC 68180-743-06

Rx Only

NIKITA (pitavastatin) tablets, 4 mg

Bottle of 30 Tablets

NDC 68180-744-06

Rx Only